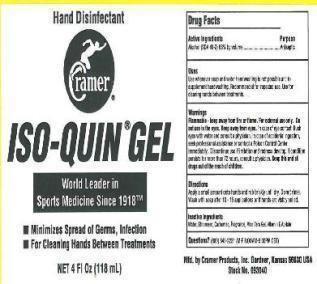 DRUG LABEL: ISO-QUIN
NDC: 11960-0550 | Form: GEL
Manufacturer: Cramer Products, Inc
Category: otc | Type: HUMAN OTC DRUG LABEL
Date: 20140730

ACTIVE INGREDIENTS: ALCOHOL 0.68 mL/1 mL
INACTIVE INGREDIENTS: WATER; PEG-15 COCAMINE; CARBOMER COPOLYMER TYPE B (ALLYL PENTAERYTHRITOL CROSSLINKED); .ALPHA.-TOCOPHEROL ACETATE; ALOE VERA LEAF

Drug Facts

Active Ingredients Purpose

Alcohol (SDA 40-2) 68% by volume.......................Antiseptic

Uses

Use whenever soap and water handwashing is not possible and to supplement handwashing. Recommended for repeated use. Use for cleaning hands between treatments.

Warnings

Flammable - keep away from fire or flame. For external use only. Do not use in the eyes. Keep away from eyes. In case of eye contact, flush eyes with water and consult a physician. In case of accidental ingestion, seek professional assistance or contact a Poison Control Center immediately. Discontinue use if irritation and redness develop. If condition persists for more than 72 hours, consult a physician.

Directions

Apply a small amount onto hands and rub briskly until dry. Do not rinse. Wash with soap after 10 - 15 applications or if hands are visibly soiled.

Inactive Ingredients

Water, Ethomeen, Carbomer, Fragrance, Aloe Vera Gel, Vitamin E Acetate

QUESTIONS

Stock No. 093042 Mfd. by Cramer Products, Inc. Gardner, Kansas 66030 USA

QUESTIONS? (800) 345-2231 (M-F 8:00AM-5:00PM CST)

KEEP OUT OF REACH OF CHILDREN

Keep this and all drugs out of the reach of children.

Purpose

Antiseptic

PACKAGE LABEL

Hand Disinfectant

World Leader in Sports Medicine Since 1918

Minimizes Spread of Germs, Infection

For Cleaning Hands Between Treatments

NET 4 Fl Oz (118 mL)